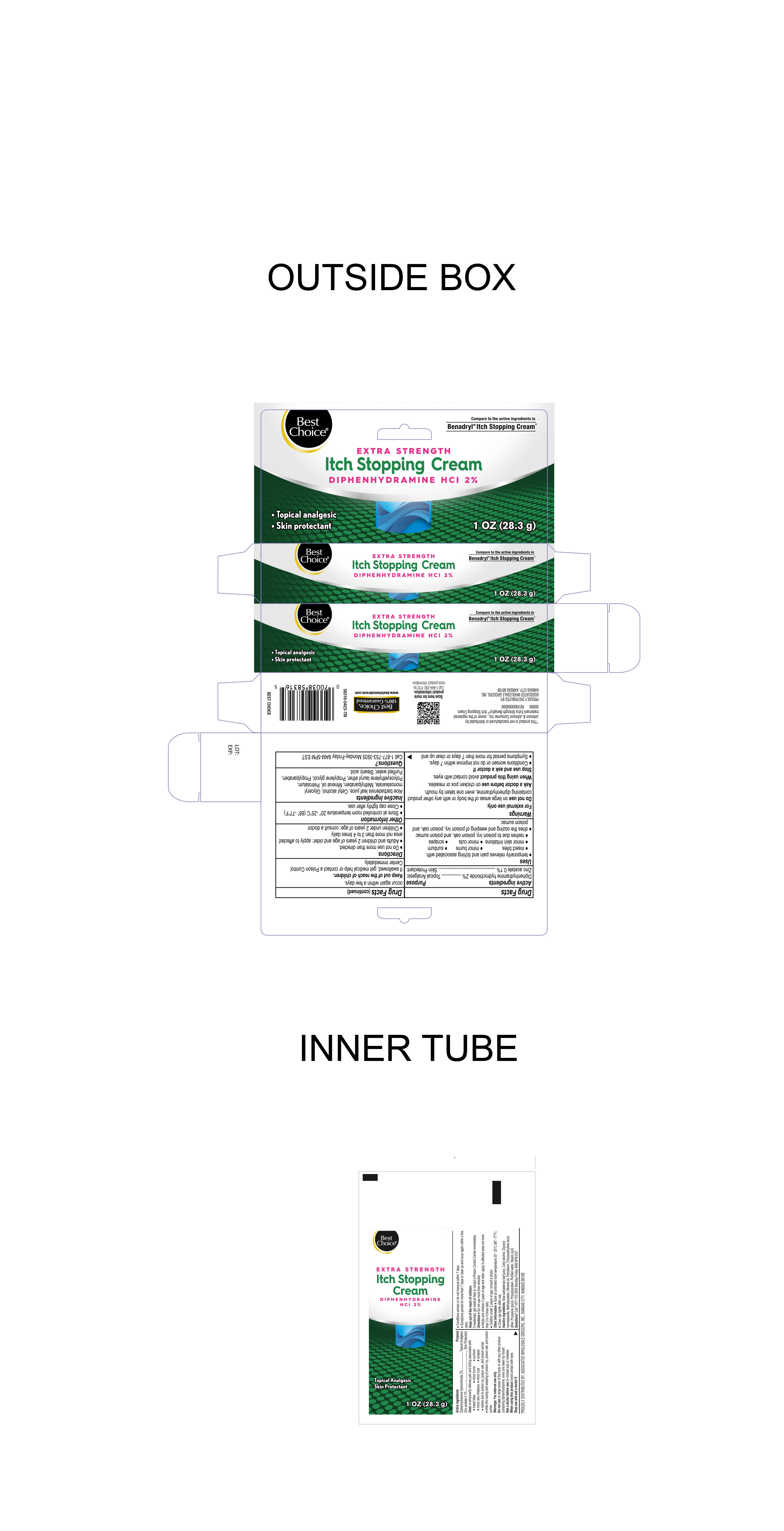 DRUG LABEL: Itch stopping Cream
NDC: 69396-150 | Form: CREAM
Manufacturer: Trifecta Pharmaceuticals USA, LLC.
Category: otc | Type: HUMAN OTC DRUG LABEL
Date: 20240212

ACTIVE INGREDIENTS: DIPHENHYDRAMINE HYDROCHLORIDE 2 g/100 g; ZINC ACETATE 0.1 g/100 g
INACTIVE INGREDIENTS: LAURETH-23; WATER; PETROLATUM; MINERAL OIL; CETYL ALCOHOL; METHYLPARABEN; PROPYLENE GLYCOL; STEARIC ACID; GLYCERYL MONOSTEARATE; PROPYLPARABEN; ALOE VERA LEAF

Best Choice Itch Stopping Cream

Active Ingredient

Diphenhydramine Hydrochloride 2%

Purpose

Topical Analgesic

Active Ingredient

Zinc Acetate 0.1%

Purpose

Skin Protectant

INDICATIONS AND USAGE

Temporarily relieves pain and itching associated with

- insect bites
- minor burns
- minor skin irritation
- sunburn
- scrapes
- rashes due to poison ivy, poison oak, and poison sumac
- dries the weeping and oozing of poison ivy, poison oak and poison sumac

Warnings

For External Use Only

Do Not Use on large areas of the body or with any other product containing diphenhydramine, even one taken by mouth.

When Using this Product avoid contact with Eyes

Stop Use and Ask a Doctor If

- Conditions worsen or do not improve within 7 days
- Symptoms presist for more than 7 days or clear up and occur again within a few days

Keep out of the reach of children

If swallowed, get medical help or contact a Poison Control Center immediately

Ask a doctor before use on chicken pox or measles

Directions

- Do not use more than directed
- Adults and children 2 years of age and older: apply to affected area not more than 3 to 4 times daily
- Children under 2 years of age: consult a doctor

Other information

- Store at controlled room temperature 20º-25ºC (68º-77ºF)
- Close cap tightly after use

Inactive Ingredients

Aloe Barbadensis leaf juice, Cetyl alcohol, Glyceryl monostearate, Methylparaben, Mineral Oil, Petrolatum, Polyoxyethylene lauryl ether, Propylene glycol, Propylparaben, Purified Water, Stearic acid

Distributed By:

Proudly Distributed by Associated Wholesale Grocers Inc.

Kansas City, KS. 66106 USA

Questions Call: 1-877-753-3935

Monday-Friday 9AM-5PM EST

This product is not manufactured or distributed by Johnson & Johnson Consumer Inc., owner of the registered trademark Extra Strength Benadryl® Itch Stopping Cream.

00000 Rev0000000000